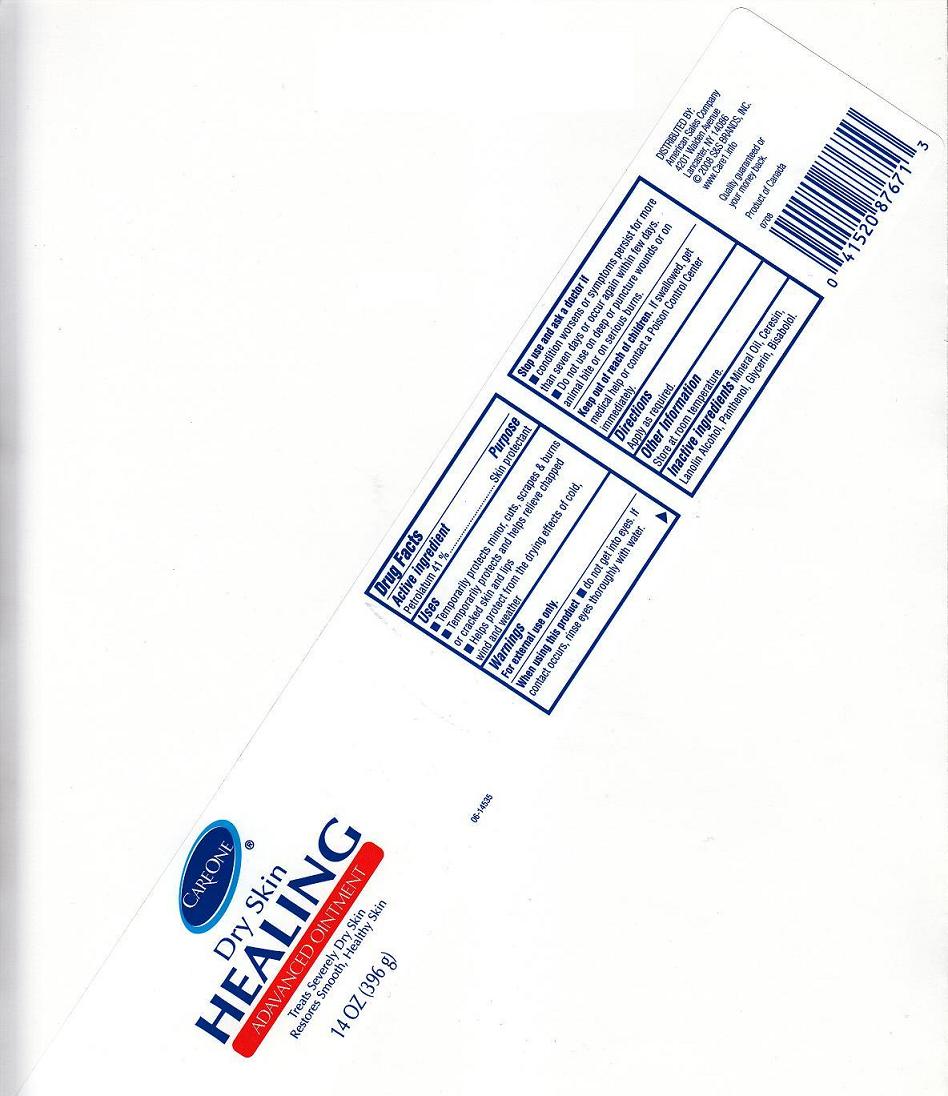 DRUG LABEL: HYDRATING HEALING
NDC: 63148-330 | Form: OINTMENT
Manufacturer: APOLLO HEALTH AND BEAUTY CARE
Category: otc | Type: HUMAN OTC DRUG LABEL
Date: 20100719

ACTIVE INGREDIENTS: PETROLATUM 41.000 g/100 g

DRUG FACTS BOX (BACK LABEL)

ACTIVE INGREDIENT

- PETROLATUM 41% (SKIN PROTECTANT)

USES AND DIRECTIONS

USES:

- TEMPORARILY PROTECTS MINOR 'CUTS' SCRAPS 'BURNS
- TEMPORARILY PROTECTS AND HELPS RELIEVE CHAPPED OR CRACKED SKIN AND LIPS
- HELPS PROTECT FROM THE DRYING EFFECTS OF COLD WIND AND WEATHER

DIRECTIONS: APPLY AS REQUIRED.

WARNINGS

- FOR EXTERNAL USE ONLY.

WHEN USING THIS PRODUCT

AVOID CONTACT WITH EYES. IF CONTACT OCCURS, RINSE EYE THOROUGHLY WITH WATER.

STOP USING THIS PRODUCT AND ASK A DOCTOR IF

CONDITION WORSENS OR SYMPTOMS PERSIST FOR MORE THAN SEVEN DAYS, OR OCCUR AGAIN WITHIN FEW DAYS.

DO NOT USE

- ON DEEP OR PUNCTURED WOUNDS, OR ON ANIMAL BITE, OR ON SERIOUS BURNS
- IF INNER SEAL IS MISSING OR BROKEN

KEEP OUT OF REACH OF CHILDREN

IN CASE OF ACCIDENTAL INGESTION, GET MEDICAL HELP OR CONTACT A POISON CONTROL CENTER IMMEDIATELY.

FRONT AND BACK LABELS

14oz front and back labels: care14.jpg